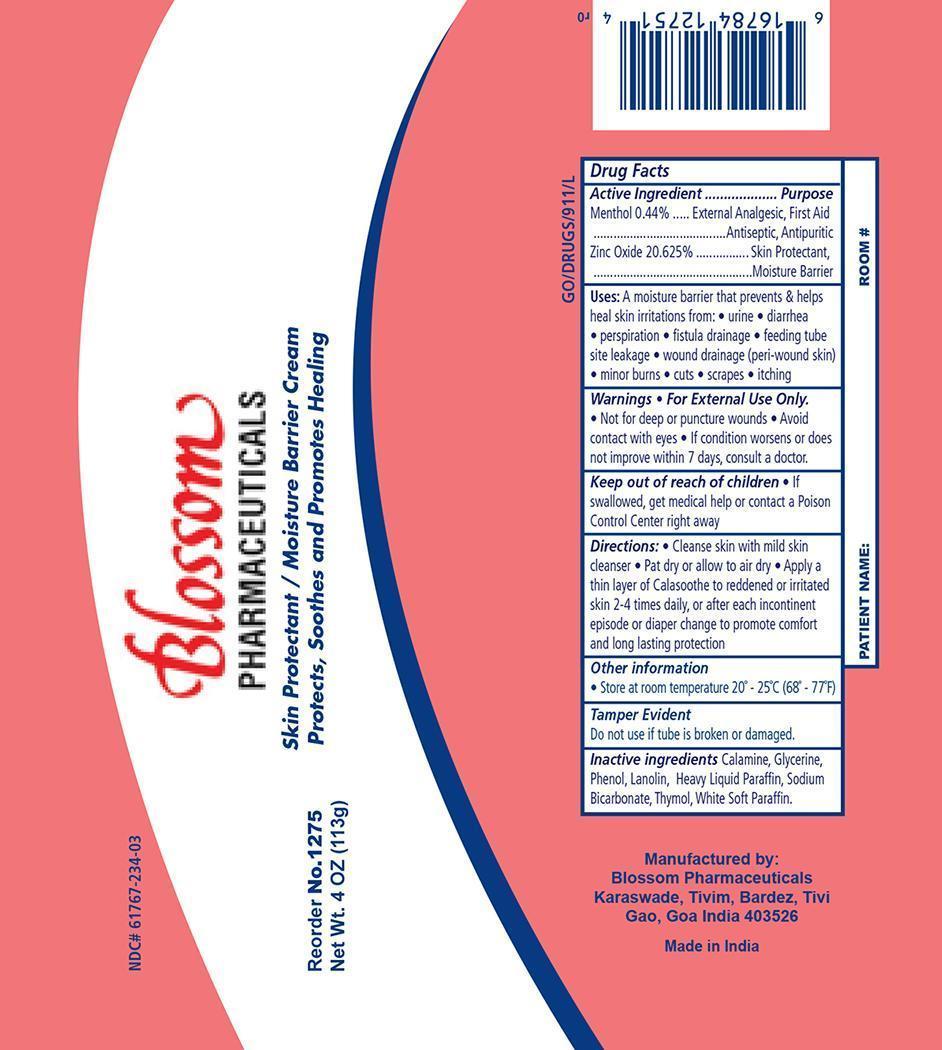 DRUG LABEL: Menthol and Zinc Oxide 
NDC: 61767-234 | Form: OINTMENT
Manufacturer: Blossom Pharmaceuticals
Category: otc | Type: HUMAN OTC DRUG LABEL
Date: 20141023

ACTIVE INGREDIENTS: MENTHOL .44 g/100 g; ZINC OXIDE 21 g/100 g
INACTIVE INGREDIENTS: GLYCERIN; PHENOL; LANOLIN; MINERAL OIL; SODIUM BICARBONATE; THYMOL; PETROLATUM

Calasoothe Ointment

Active Ingredient Purpose

Menthol 0.44% v/v External Analgesic

First Aid Antiseptic

Antipuritic

Zinc Oxide 20.625% v/v Skin Protectant

Moisture Barrier

Purpose:

A moisture barrier that prevents and helps heal skin irritations from;

- urine
- diarrhea
- perspiration
- fistula drainage
- feeding tube site leakage
- wound drainage (peri-wound skin)
- minor burns
- cuts
- scrapes
- itching

Warnings:

Keep out of reach of children

- If swallowed, get medical help or contact a Poison Control Center right away.

Indications & Usage

- Not for deep or puncture wounds.
- Avoid contact with eyes.
- If condition worsens or does not improve within 7 days, consult a doctor

Dosage & Administration:

- Clean skin with mild skin cleanser
- Pat dry or allow to air dry
- Apply a thin layer of Calasoothe to reddened or irritated skin 2-4 times daily, or after each incontinent episode or diaper change to promote comfort and long lasting protection

Keep Out Of Reach Of Children

If swallowed , get medical help or contact a Poison Control Center right away.

Inactive Ingredients

Inactive Ingredients: Calamine, Glycerine, Phenol, Lanolin, Heavy Liquid Paraffin, Sodium Bicarbonate, Thymol, White Soft Paraffin

Principal Display Panel - Ointment

Blossom1275.jpg